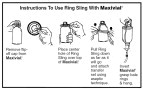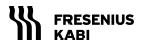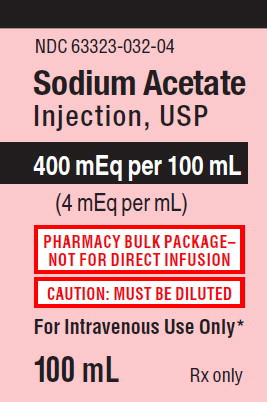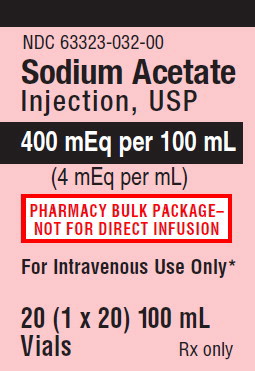 DRUG LABEL: SODIUM ACETATE
NDC: 63323-032 | Form: INJECTION, SOLUTION, CONCENTRATE
Manufacturer: Fresenius Kabi USA, LLC
Category: prescription | Type: HUMAN PRESCRIPTION DRUG LABEL
Date: 20241011

ACTIVE INGREDIENTS: SODIUM ACETATE 4 meq/100 mL
INACTIVE INGREDIENTS: WATER; ACETIC ACID

Sodium Acetate Injection, USP

451406/Issued: December 2017

Sodium Acetate

Injection, USP

Rx only

PHARMACY BULK PACKAGE—

NOT FOR DIRECT INFUSION

FOR ADDITIVE USE ONLY AFTER DILUTION IN INTRAVENOUS FLUIDS.

DESCRIPTION:

Sodium Acetate Injection, USP (4 mEq per mL) is a sterile, nonpyrogenic, concentrated solution of sodium acetate in water for injection. The solution is administered after dilution by the intravenous route as an electrolyte replenisher. It must not be administered undiluted. Each mL contains: 328 mg sodium acetate (anhydrous) which provides 4 mEq each of sodium (Na^+) and acetate (CH3COO^-). The solution contains no bacteriostat, antimicrobial agent or added buffer. The pH may have been adjusted with glacial acetic acid to 6.5 (6.0 to 7.0). The osmolar concentration is 8 mOsmol/mL (calc); specific gravity 1.1511.

The solution is intended as an alternative to sodium chloride to provide sodium ion (Na^+) for addition to large volume infusion fluids for intravenous use.

Sodium acetate, USP anhydrous is chemically designated as CH3COONa, a hygroscopic powder very soluble in water.

A Pharmacy Bulk Package is a container of a sterile preparation for parenteral use that contains many single doses. The contents are intended for use in a pharmacy admixture program and are restricted to the preparation of admixtures for intravenous infusion.

CLINICAL PHARMACOLOGY:

Sodium is the principal cation of extracellular fluid. It comprises more than 90% of total cations at its normal plasma concentration of approximately 140 mEq/L. The sodium ion exerts a primary role in controlling total body water and its distribution.

Acetate (CH3COO^-) is a hydrogen ion acceptor. It also serves as an alternate source of bicarbonate (HCO3^-) by metabolic conversion in the liver. This conversion has been shown to proceed readily, even in the presence of severe liver disease.

INDICATIONS AND USAGE:

Sodium Acetate Injection, USP (4 mEq per mL) is indicated as a source of sodium for addition to large volume intravenous fluids to prevent or correct hyponatremia in patients with restricted or no oral intake. It is also useful as an additive for preparing specific intravenous fluid formulas when the needs of the patient cannot be met by standard electrolyte or nutrient solutions.

CONTRAINDICATIONS:

Sodium Acetate Injection, USP (4 mEq per mL) is contraindicated in patients with hypernatremia or fluid retention.

WARNINGS:

Sodium Acetate Injection, USP (4 mEq per mL) must be diluted before use.

To avoid sodium overload and water retention, infuse sodium-containing solutions slowly.

Solutions containing sodium ions should be used with great care, if at all, in patients with congestive heart failure, severe renal insufficiency and in clinical states in which there exists edema with sodium retention.

In patients with diminished renal function, administration of solutions containing sodium ions may result in sodium retention.

Solutions containing acetate ions should be used with great care in patients with metabolic or respiratory alkalosis. Acetate should be administered with great care in those conditions in which there is an increased level or an impaired utilization of this ion, such as severe hepatic insufficiency.

The intravenous administration of this solution (after appropriate dilution) can cause fluid and/or solute overloading resulting in dilution of other serum electrolyte concentrations, overhydration, congested states or pulmonary edema. Excessive administration of potassium free solutions may result in significant hypokalemia.

WARNING: This product contains aluminum that may be toxic. Aluminum may reach toxic levels with prolonged parenteral administration if kidney function is impaired. Premature neonates are particularly at risk because their kidneys are immature, and they require large amounts of calcium and phosphate solutions, which contain aluminum.

Research indicates that patients with impaired kidney function, including premature neonates, who receive parenteral levels of aluminum at greater than 4 to 5 mcg/kg/day accumulate aluminum at levels associated with central nervous system and bone toxicity. Tissue loading may occur at even lower rates of administration.

PRECAUTIONS:

Do not administer unless solution is clear and seal is intact. Discard unused portion.

Sodium replacement therapy should be guided primarily by the serum sodium level.

Caution should be exercised in administering sodium-containing solutions to patients with severe renal function impairment, cirrhosis, cardiac failure or other edematous or sodium-retaining states, as well as in patients with oliguria or anuria.

Caution must be exercised in the administration of parenteral fluids, especially those containing sodium ions, to patients receiving corticosteroids or corticotropin.

Solutions containing acetate ions should be used with caution as excess administration may result in metabolic alkalosis.

Pregnancy

Pregnancy Category C

Animal reproduction studies have not been conducted with Sodium Acetate Injection, USP. It is also not known whether Sodium Acetate Injection, USP can cause fetal harm when administered to a pregnant woman or can affect reproduction capacity. Sodium Acetate Injection, USP should be given to a pregnant woman only if clearly needed.

Pediatric Use

Safety and effectiveness have been established in the age groups infant to adolescent.

Geriatric Use

An evaluation of current literature revealed no clinical experience identifying differences in response between elderly and younger patients. In general, dose selection for an elderly patient should be cautious, usually starting at the low end of the dosing range, reflecting the greater frequency of decreased hepatic, renal, or cardiac function, and of concomitant disease or other drug therapy.

Sodium ions are known to be substantially excreted by the kidney, and the risk of toxic reactions may be greater in patients with impaired renal function. Because elderly patients are more likely to have decreased renal function, care should be taken in dose selection, and it may be useful to monitor renal function.

ADVERSE REACTIONS:

Sodium overload can occur with intravenous infusion of excessive amounts of sodium-containing solutions (see WARNINGS and PRECAUTIONS).

OVERDOSAGE:

In the event of overdosage, discontinue infusion containing sodium acetate immediately and institute corrective therapy as indicated to reduce elevated serum sodium levels, and restore acid-base balance if necessary (see WARNINGS, PRECAUTIONS and ADVERSE REACTIONS).

DOSAGE AND ADMINISTRATION:

Sodium Acetate Injection, USP (4 mEq per mL) is administered intravenously only after dilution in a larger volume of fluid. The dose and rate of administration are dependent upon the individual needs of the patient. Serum sodium should be monitored as a guide to dosage. Using aseptic technique, transfer the desired amount to other intravenous fluids to provide the appropriate number of milliequivalents (mEq) of sodium acetate.

Sodium Acetate Injection, USP (4 mEq per mL) in the Pharmacy Bulk Package is designed for use with manual, gravity flow operations and automated compounding devices for preparing intravenous nutritional admixtures. Admixtures must be stored under refrigeration and used within 24 hours after compounding.

Parenteral drug products should be inspected visually for particulate matter and discoloration prior to administration (see PRECAUTIONS).

Directions for Dispensing from Pharmacy Bulk Package

The Pharmacy Bulk Package is for use in the Pharmacy Admixture Service only in a laminar flow hood. It should be inserted into the ring sling (plastic hanging device) provided and suspended as a unit in the laminar flow hood. The container closure should be penetrated only one time utilizing a suitable sterile dispensing set which allows measured distribution of the contents. Swab vial stopper with an antiseptic solution. Insert the dispensing set into the vial using aseptic technique (see graphic illustration below).

Once the sterile dispensing set has been inserted into the container, withdrawal of the contents should be accomplished without delay. However, if this is not possible, a maximum time of 4 hours from the initial entry may be allowed to complete fluid aliquoting/transferring operations. Discard the container no later than 4 hours after initial closure puncture.

Do not administer unless solution is clear and seal is intact.

HOW SUPPLIED:

Sodium Acetate Injection, USP is packaged in a pharmacy bulk package vial, 20 vials per tray, and is available as follows:

Product No. | NDC No. | Sodium Acetate Content (%) | Na^+ (sodium) mEq/mL | CH 3 COO^-(acetate) mEq/mL | mOsmol/mL | Fill Vol. (mL)
322100 | 63323-032-00 | 32.8 | 4 | 4 | 8 | 100

Store at 20° to 25°C (68° to 77°F) [See USP Controlled Room Temperature].

Lake Zurich, IL 60047
www.fresenius-kabi.com/us

451406
Issued: December 2017

PACKAGE LABEL - PRINCIPAL DISPLAY – Sodium Acetate 400 mEq per 100 mL Vial Label

NDC 63323-032-04

Sodium Acetate

Injection, USP

400 mEq per 100 mL

(4 mEq per mL)

PHARMACY BULK PACKAGE–

NOT FOR DIRECT INFUSION

CAUTION: MUST BE DILUTED

For Intravenous Use Only

100 mL Rx only

PACKAGE LABEL - PRINCIPAL DISPLAY – Sodium Acetate 400 mEq per 100 mL Tray Label

NDC 63323-032-00

Sodium Acetate

Injection, USP

400 mEq per 100 mL

(4 mEq per mL)

PHARMACY BULK PACKAGE–

NOT FOR DIRECT INFUSION

For Intravenous Use Only

20 (1 x 20) 100 mL Vials Rx only